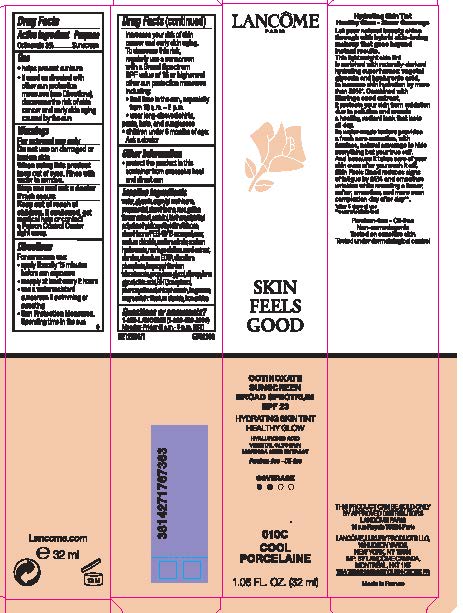 DRUG LABEL: Lancome Paris Skin Feels Good Broad Spectrum SPF 23 Sunscreen Hydrating Skin Tint Healthy Glow
NDC: 51150-736 | Form: LIQUID
Manufacturer: SICOS ET CIE
Category: otc | Type: HUMAN OTC DRUG LABEL
Date: 20231223

ACTIVE INGREDIENTS: Octinoxate 30 mg/1 mL
INACTIVE INGREDIENTS: WATER; GLYCERIN; CAPRYLYL TRISILOXANE; PROPANEDIOL; DIMETHICONE; ROSA GALLICA FLOWER; SORBITOL; SODIUM CHLORIDE; SODIUM CITRATE; HYALURONATE SODIUM; MORINGA OLEIFERA LEAF; ALUMINUM OXIDE; EDETATE DISODIUM; SODIUM PHOSPHATE, DIBASIC, ANHYDROUS; ISOPROPYL TITANIUM TRIISOSTEARATE; PROPYLENE GLYCOL; DIPROPYLENE GLYCOL; CITRIC ACID MONOHYDRATE; BUTYLATED HYDROXYTOLUENE; TOCOPHEROL; PHENOXYETHANOL; CHLORPHENESIN; TITANIUM DIOXIDE; FERRIC OXIDE RED

Drug Facts

Active ingredient

Octinoxate 3%

Purpose

Sunscreen

Uses

- helps prevent sunburn
- if used as directed with other sun protection measures (see Directions), decreases the risk of skin cancer and early skin aging caused by the sun

Warnings

For external use only

Flammable until dry.

Do not use near fire, flame or heat.

Do not use

on damaged or broken skin

When using this product

keep out of eyes. Rinse with water to remove.

Stop use and ask a doctor if

rash occurs

Keep out of reach of children.

If swallowed, get medical help or contact a Poison Control Center right away.

Directions

For sunscreen use:

● shake well

● apply liberally 15 minutes before sun exposure

● reapply at least every 2 hours

● use a water resistant sunscreen if swimming or sweating

● Sun Protection Measures. Spending time in the sun increases your risk of skin cancer and early skin aging. To decrease this risk, regularly use a sunscreen with a Broad Spectrum SPF value of 15 or higher and other sun protection measures including:

● limit time in the sun, especially from 10 a.m. – 2 p.m.

● wear long-sleeved shirts, pants, hats, and sunglasses

● children under 6 months of age: Ask a doctor

Other information

protect the product in this container from excessive heat and direct sun

Inactive ingredients

water, glycerin, caprylyl methicone, propanediol, dimethicone, rosa gallica flower exract, sorbitol, triethoxysilylethyl polydimethylsiloxyethyl dimethicone, dimethicone/PEG-10/15 crosspolymer, sodium chloride, sodium citrate, sodium hyaluronate, morninga oleifera seed extract, alumina, disodium EDTA, disodium phosphate, isopropyl titanium triisostearate, propylene glycol, diproplylene glycol, citric acid, BHT, tocopherol, phenoxyethanol, chlorphenesin, fragrance; may contain: titanium dioxide, iron oxides

Questions or comments?

1-800-LANCOME

(1-800-526-2663)

Monday - Friday (9 a.m. - 5 p.m. EST)